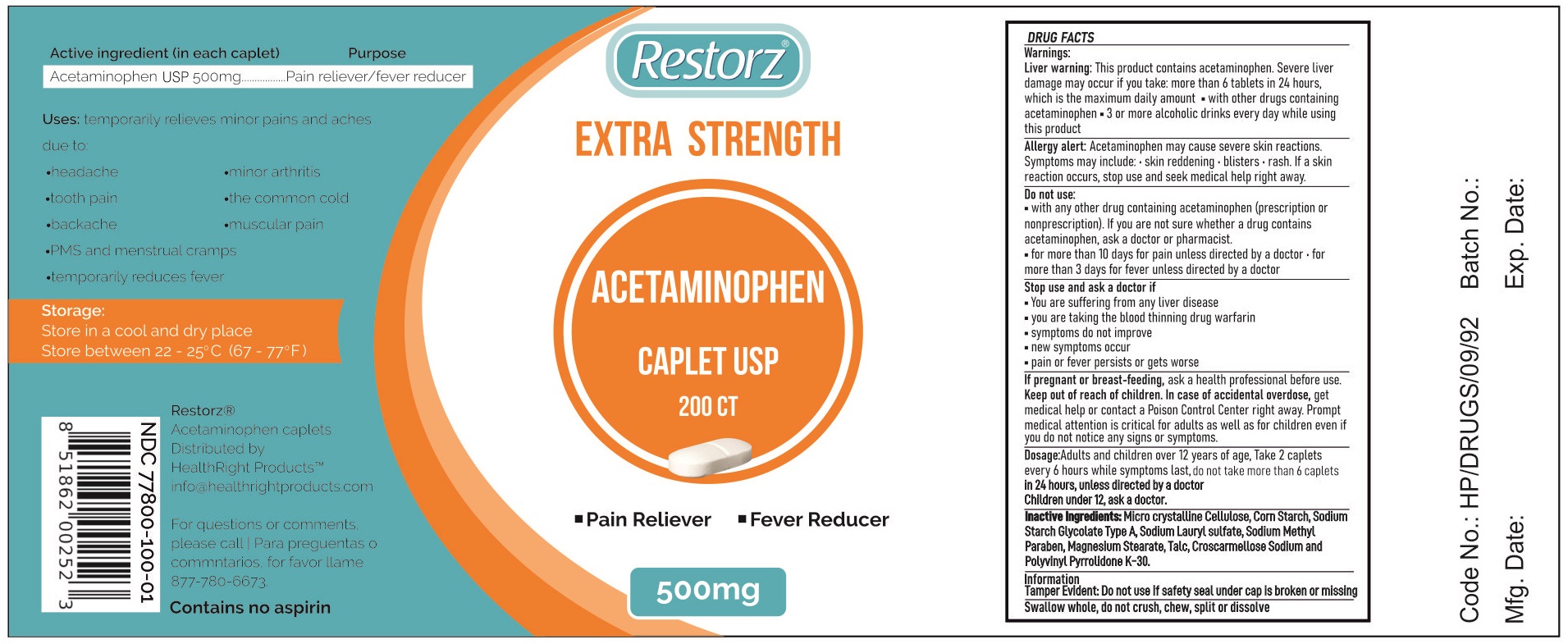 DRUG LABEL: Acetaminophen
NDC: 77800-100 | Form: TABLET
Manufacturer: HealthRight Products, LLC
Category: otc | Type: HUMAN OTC DRUG LABEL
Date: 20200728

ACTIVE INGREDIENTS: Acetaminophen 500 mg/1 1
INACTIVE INGREDIENTS: MICROCRYSTALLINE CELLULOSE; STARCH, CORN; SODIUM STARCH GLYCOLATE TYPE A; SODIUM LAURYL SULFATE; METHYLPARABEN SODIUM; MAGNESIUM STEARATE; TALC; CROSCARMELLOSE SODIUM; POVIDONE K30

Acetaminophen 500 mg Extra Strength

Important: Read all product information before using. Keep this box for important information.

Drug Facts

Active ingredient (in each caplet)

Acetaminophen USP 500 mg

Purpose

Pain reliever/fever reducer

Uses

temporarily relieves minor aches and pains due to

- headache
- tooth pain
- backache
- PMS and menstrual cramps
- temporarily reduces fever
- minor arthritis
- the common cold
- muscular pain

Warnings

Liver warning: This product contains acetaminophen. Severe liver damage may occur if you take: more than 6 tablets in 24 hours, which is the maximum daily amount

- with other drugs containing acetaminophen
- 3 or more alcoholic drinks every day while using this product

Allergy alert: Acetaminophen may cause severe skin reaction. Symptoms may include:

- skin reddening
- blisters
- rash

If a skin reaction occurs, stop use and seek medical help right away.

Do not use

- with any other drug containing acetaminophen (prescription or nonprescription). If you are not sure whether a drug contains acetaminophen, ask a doctor or pharmacist.
- for more than 10 days for pain unless directed by a doctor
- for more than 3 days for fever unless directed by a doctor

Stop use and ask a doctor if

- You are suffering from any liver disease
- you are taking the blood thinning drug warfarin
- symptoms do not improve
- new symptoms occur
- pain or fever persists or gets worse

PREGNANCY OR BREAST FEEDING

If pregnant or breast-feeding, ask a health professional before use.

Keep out of reach of children.

OVERDOSAGE

In case of accidental overdose, get medical help or contact a Poison Control Center right away. Prompt medical attention is critical for adults as well as for children even if you do not notice any signs or symptoms.

Dosage

Adults and children over 12 years of age, Take 2 caplets every 6 hours while symptoms last, do not take more than 6 caplets in 24 hours, unless directed by a doctor.
Children under 12, ask a doctor.

Storage

- Store in a cool and dry place
- Store between 22-25˚C (67-77˚F)

Inactive ingredients

Micro crystalline Cellulose, Corn Starch, Sodium Starch Glycolate Type A, Sodium Lauryl sulfate, Sodium Methyl Paraben, Magnesium Stearate, Talc, Croscarmellose Sodium and polyvinyl pyrrolidone K-30

Information

Tamper Evident: Do not use if safety seal under cap is broken or missing

Swallow whole, do not crush, chew, split or dissolve

PRINCIPAL DISPLAY PANEL - 200 CT

Acetaminophen Caplet, 500 mg

Pain Reliever - Fever Reducer